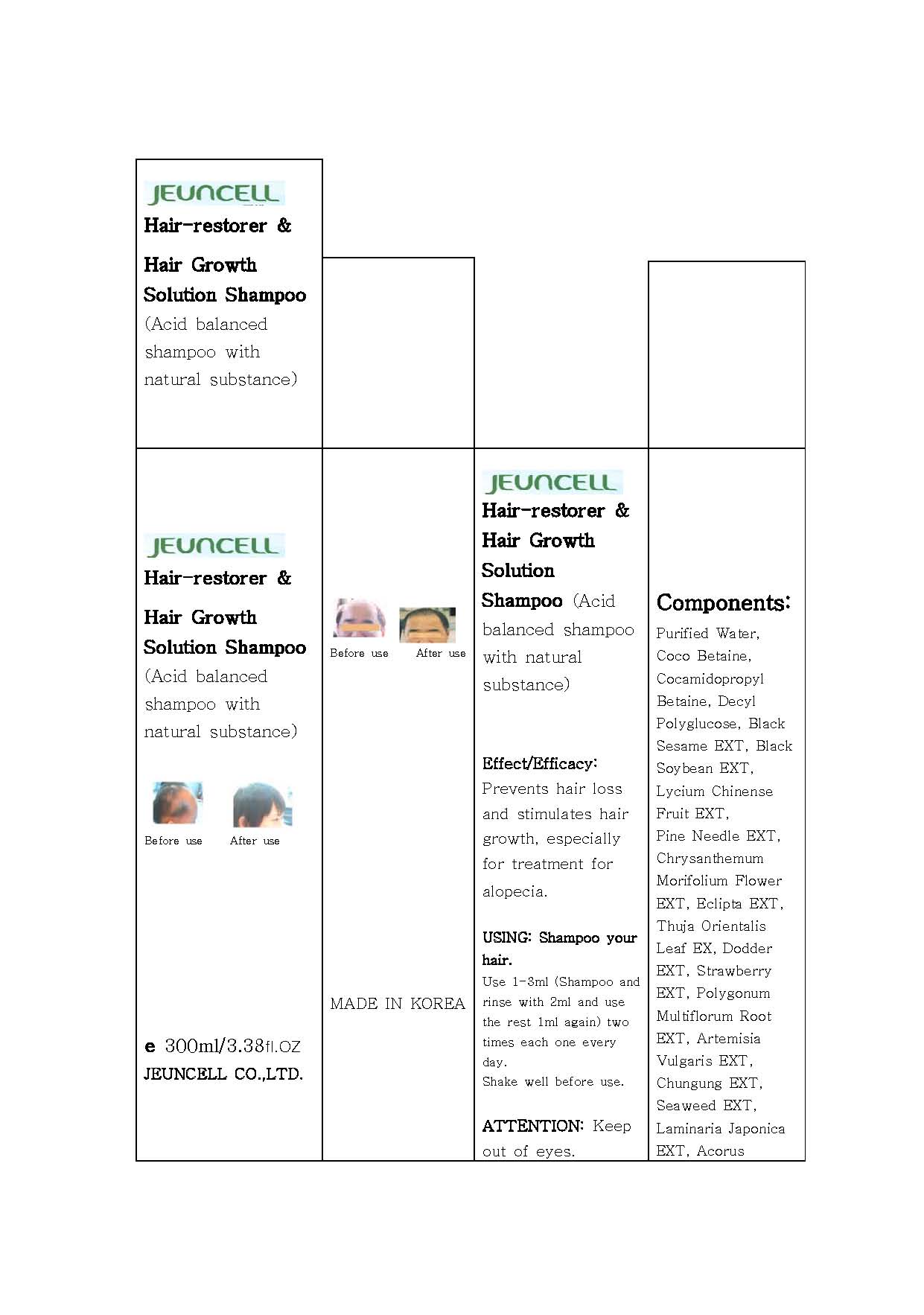 DRUG LABEL: JEUNCELL Hair restorer and Hair Growth Solution
                
NDC: 54296-3001 | Form: SHAMPOO
Manufacturer: Jeun Cell Ltd
Category: otc | Type: HUMAN OTC DRUG LABEL
Date: 20121125

ACTIVE INGREDIENTS: NIACIN 2 mg/100 mL
INACTIVE INGREDIENTS: PINE NEEDLE OIL (PINUS MUGO); TRIPTERYGIUM WILFORDII ROOT; COCAMIDOPROPYL BETAINE; SESAME OIL; LYCIUM CHINENSE FRUIT; CHRYSANTHEMUM X MORIFOLIUM FLOWER; ECLIPTA PROSTRATA WHOLE; PLATYCLADUS ORIENTALIS LEAF; STRAWBERRY; FALLOPIA MULTIFLORA ROOT; ARTEMISIA VULGARIS ROOT; NORI; LAMINARIA JAPONICA; ACORUS CALAMUS ROOT; CAPSICUM; GREEN TEA LEAF; ASIAN GINSENG; JOJOBA OIL; DEXPANTHENOL; ROSEMARY; SODIUM BENZOATE

Drug Facts

ACTIVE INGREDIENT

nicotinic acid amide

INACTIVE INGREDIENT

purified water, coco betaine, cocamidopropyl betaine, decyl polyglucose, black sesame ext, black soybean ext, lycium chinense fruit ext, pine needle ext, chrysanthemum morifolium flower ext, eclipta ext, thuja orientalis leaf ext, dodder ext, strawberry ext, polygonum multiflorim root ext, artemisia vulgaris ext, chungung ext, seaweed ext, laminaria japonica ext, acorus

PURPOSE

to prevent hair loss and stimulates hair growth, especially for treatment for alopecia

keep out of reach of the children

INDICATIONS AND USAGE

■ Shampoo your hair
■ Use 1-3ml (Shampoo and rinse with 2ml and use the rest 1ml again) two times each one every day.

WARNINGS

- keep out of eyes

DOSAGE AND ADMINISTRATION

for external use only